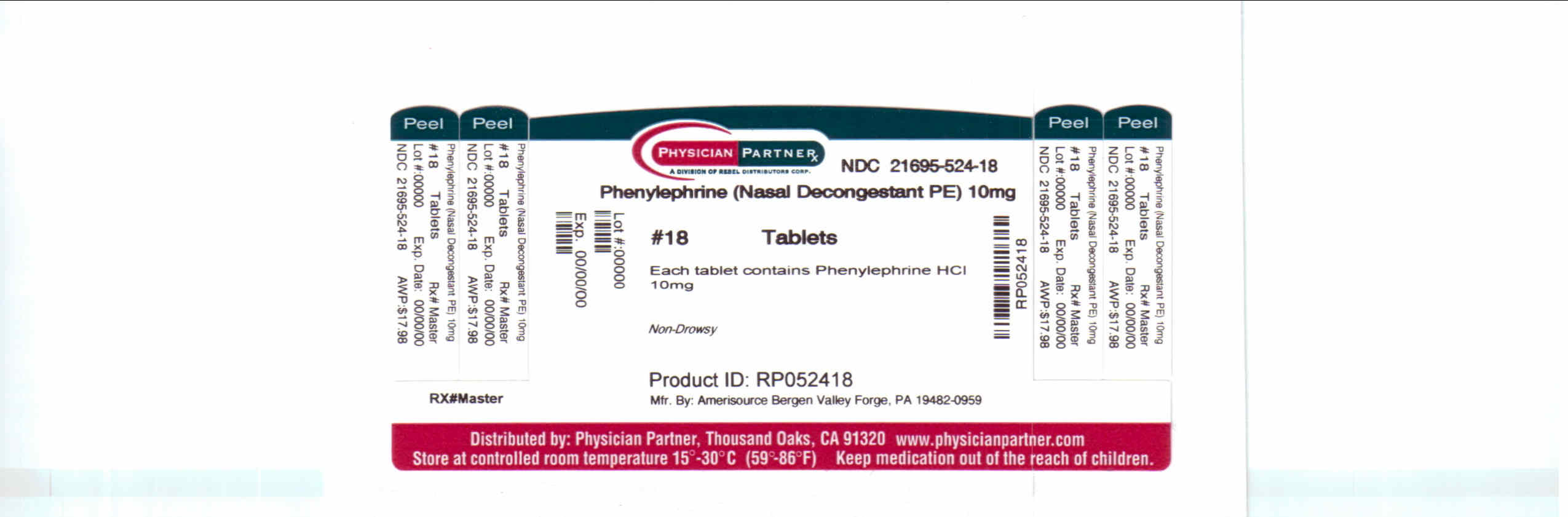 DRUG LABEL: Phenylephrine
NDC: 21695-524 | Form: TABLET
Manufacturer: Rebel Distributors Corp
Category: otc | Type: HUMAN OTC DRUG LABEL
Date: 20110221

ACTIVE INGREDIENTS: PHENYLEPHRINE HYDROCHLORIDE 10 mg/1 1
INACTIVE INGREDIENTS: CARNAUBA WAX; ANHYDROUS DIBASIC CALCIUM PHOSPHATE; FD&C RED NO. 40; LECITHIN, SOYBEAN; MAGNESIUM STEARATE; CELLULOSE, MICROCRYSTALLINE; POLYETHYLENE GLYCOL; POLYVINYL ALCOHOL; SILICON DIOXIDE; TALC; TITANIUM DIOXIDE

Phenylephrine Drug Facts

Active ingredient

Phenylephrine hydrochloride 10 mg

Purpose

Nasal decongestant

Keep Out of Reach of Children

In case of overdose, get medical help or contact a Poison Control Center right away.

Uses

° temporarily relieves sinus congestion and pressure

° temporarily relieves nasal congestion due to the common cold, hay fever or other upper respiratory allergies

Warnings

Do not use if you are now taking a prescription monoamine exidase inhibitor (MAOI) (certain drugs for depression, psychiatric or emotional conditions, or Parkinson's disease), or for 2 weeks after stopping the MAOI drug. If you do not know if your prescription drug contains an MAOI, ask a doctor or pharmacist before taking this product.

Ask a doctor before use if you have:

° heart disease ° high blood pressure ° diabetes ° trouble urinating due to an enlarge prostate gland ° thyroid disease

When using this product, do not use more than directed.

Stop use and ask a doctor if:

° you get nervous, dizzy or sleepless

° symptoms do not improve within 7 days or are accompanied by fever

If pregnant or breast-feeding, ask a health professional before use.

Directions

° take every 4 hours

° do not take more than 6 doses in 24 hours

° adults and children 12 years of age and over: 1 tablet

° children under 12 years of age: ask a doctor

Other information

Store at room temperature (59°-86°F)

Inactive ingredients

carnauba wax. dibasic calcium phosphate, FD&C red no. 40, lecithin, magnesium stearate, microcrystalline cellulose, polyethylene glycol, polyvinyl alcohol, silicon dioxide, talc, titanium dioxide